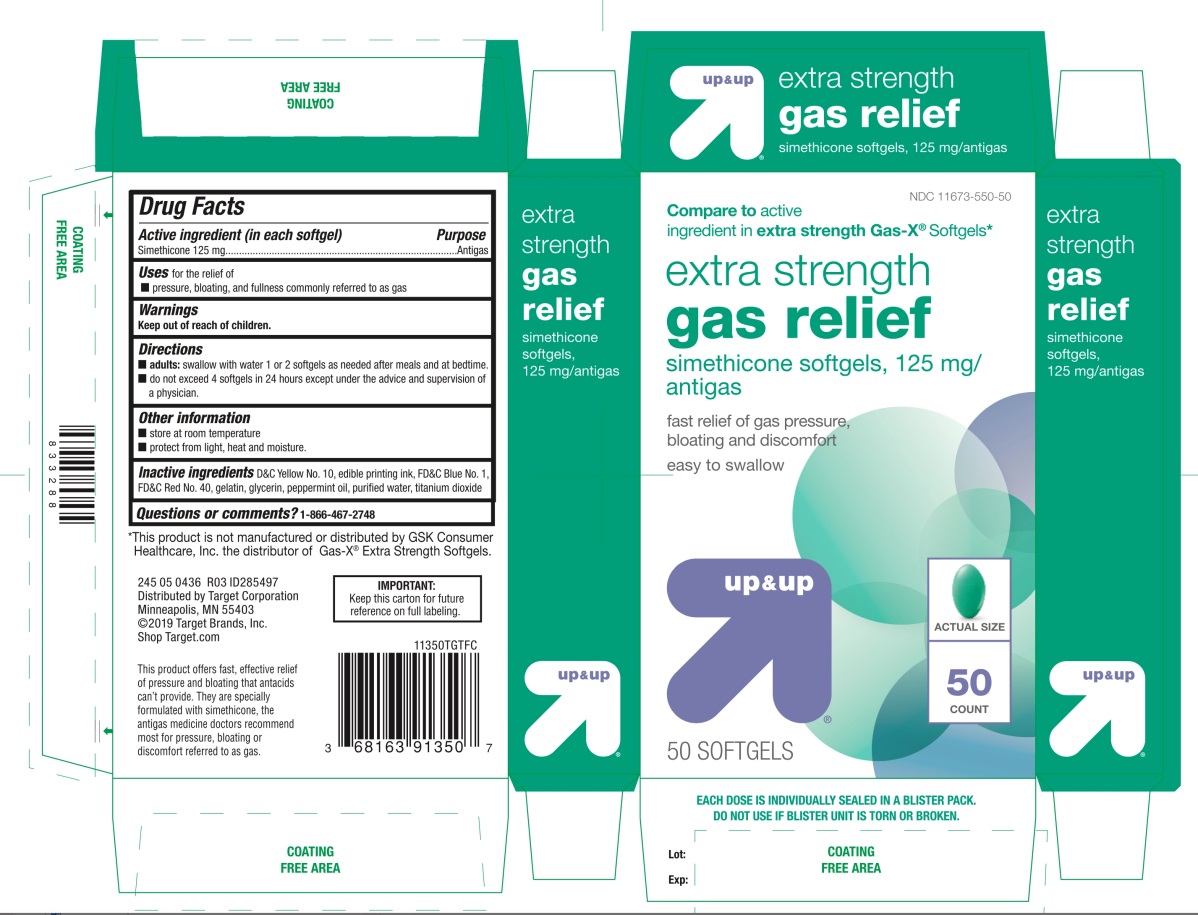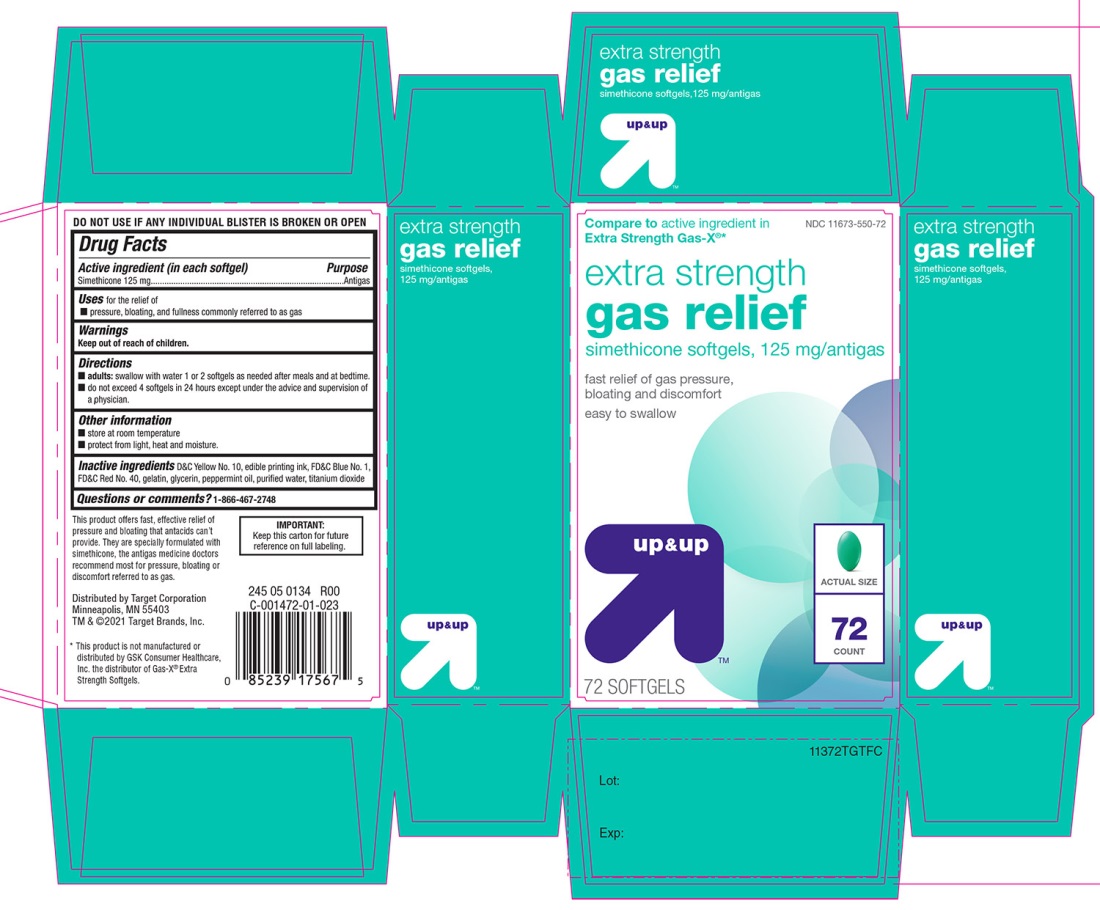 DRUG LABEL: Gas Relief

NDC: 11673-550 | Form: CAPSULE, LIQUID FILLED
Manufacturer: Target Corporation
Category: otc | Type: HUMAN OTC DRUG LABEL
Date: 20251104

ACTIVE INGREDIENTS: DIMETHICONE, UNSPECIFIED 125 mg/1 1
INACTIVE INGREDIENTS: D&C YELLOW NO. 10; FD&C BLUE NO. 1; FD&C RED NO. 40; GELATIN, UNSPECIFIED; GLYCERIN; PEPPERMINT OIL; WATER; TITANIUM DIOXIDE

Extra Strength Gas Relief Softgels

Active ingredient (in each softgel)

Simethicone 125 mg

Purpose

Antigas

Uses for the relief

- pressure, bloating, and fullness commonly referred to as gas

Directions

- adults: swallow with water 1 or 2 softgels as needed after meals and at bedtime
- do not exceed 4 softgels in 24 hours except under the advice and supervision of a physician

Other information

- store at room temperature
- protect from light, heat, and moisture

Inactive ingredients

D&C Yellow No. 10, edible printing ink, FD&C Blue No.1, FD&C Red No. 40, gelatin, glycerin, peppermint oil, purified water, titanium dioxide

Questions or comments?

1-866-467-2748

Principal Display Panel

Compare to active ingredient in Extra Strength Gas-X® Softgels*

Extra Strength

Gas Relief

Simethicone softgels 125 mg/ antigas

fast relief of gas pressure, bloating and discomfort

easy to swallow

up & up

DO NOT USE IF ANY INDIVIDUAL BLISTER IS BROKEN OR OPEN.

IMPORTANT:Keep this carton for future reference on full labeling

**This product is not manufactured or distributed by GSK Consumer Healthcare, Inc. the distributor of Gas-X®Extra Strength Softgels.

Distributed by Target Corporation

Minneapolis, MN 55403

TM & © 2021 Target Brands, Inc.

Shop Target.com

This product offers fast, effective relief of pressure and bloating that antacids can’t provide.

They are specially formulated with simethicone, the antigas medicine doctors recommends most for pressure, bloating or discomfort referred to as gas.